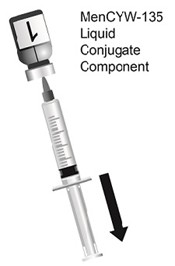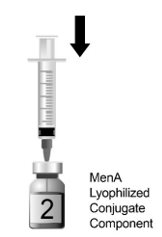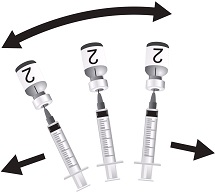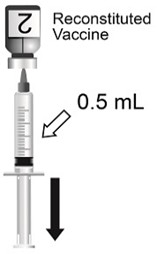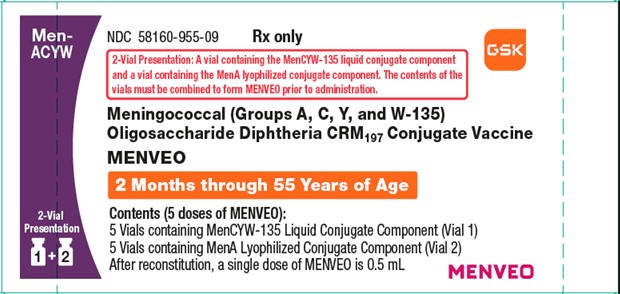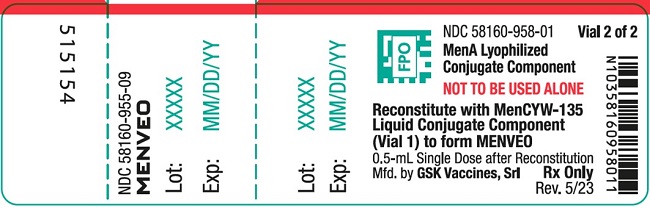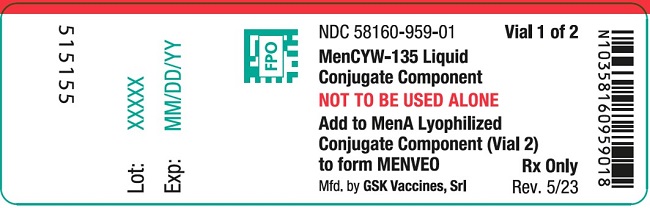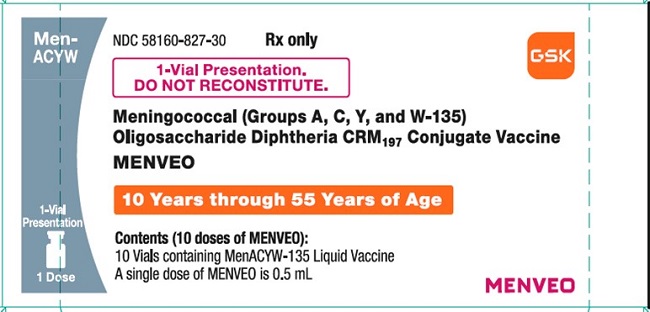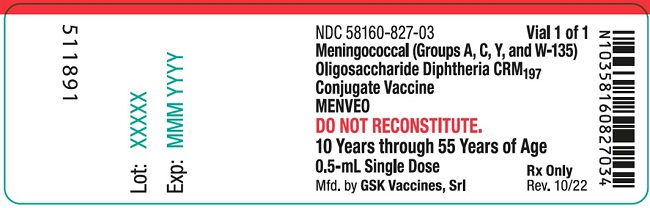 DRUG LABEL: Menveo
NDC: 58160-955 | Form: KIT | Route: INTRAMUSCULAR
Manufacturer: GlaxoSmithKline Biologicals SA
Category: other | Type: VACCINE LABEL
Date: 20250331

ACTIVE INGREDIENTS: NEISSERIA MENINGITIDIS GROUP A CAPSULAR OLIGOSACCHARIDE DIPHTHERIA CRM197 PROTEIN CONJUGATE ANTIGEN 10 ug/0.5 mL; NEISSERIA MENINGITIDIS GROUP C CAPSULAR OLIGOSACCHARIDE DIPHTHERIA CRM197 PROTEIN CONJUGATE ANTIGEN 5 ug/0.5 mL; NEISSERIA MENINGITIDIS GROUP W-135 CAPSULAR OLIGOSACCHARIDE DIPHTHERIA CRM197 PROTEIN CONJUGATE ANTIGEN 5 ug/0.5 mL; NEISSERIA MENINGITIDIS GROUP Y CAPSULAR OLIGOSACCHARIDE DIPHTHERIA CRM197 PROTEIN CONJUGATE ANTIGEN 5 ug/0.5 mL
INACTIVE INGREDIENTS: Sucrose; MONOBASIC POTASSIUM PHOSPHATE; Sodium chloride; Sodium Phosphate, Monobasic, Monohydrate; SODIUM PHOSPHATE, DIBASIC, DIHYDRATE

HIGHLIGHTS OF PRESCRIBING INFORMATION

These highlights do not include all the information needed to use MENVEO safely and effectively. See full prescribing information for MENVEO.
MENVEO [Meningococcal (Groups A, C, Y, and W-135) Oligosaccharide Diphtheria CRM197 Conjugate Vaccine] solution for injection, for intramuscular use
Initial U.S. Approval: 2010

RECENT MAJOR CHANGES

Dosage and Administration, Preparation (2.2) | 03/2025

1 INDICATIONS AND USAGE

MENVEO is a vaccine indicated for active immunization to prevent invasive meningococcal disease caused by Neisseria meningitidis serogroups A, C, Y, and W-135 in individuals 2 months through 55 years of age.

MENVEO does not prevent N. meningitidis serogroup B infections. (1)

2 DOSAGE AND ADMINISTRATION

- For intramuscular injection only (0.5 mL). (2)
MENVEO is supplied as either:
- Two vials: A vial containing the MenCYW-135 liquid conjugate component (gray cap) and a vial containing the MenA lyophilized conjugate component (orange cap). The contents of the vials must be combined to form MENVEO prior to administration. This presentation is for use in individuals 2 months through 55 years of age. (2.1, 2.2),
OR
- One vial containing MENVEO (pink cap). This presentation does not require reconstitution before use. This presentation is for use in individuals 10 through 55 years of age. (2.1, 2.2)

Primary Vaccination

- In children initiating vaccination at 2 months of age, administer as a 4-dose series at 2, 4, 6, and 12 months of age. (2.4)
- In children initiating vaccination at 7 months through 23 months of age, administer as a 2-dose series with the second dose administered in the second year of life and at least 3 months after the first dose. (2.4)
- In individuals aged 2 through 55 years, administer as a single dose. (2.4)

Booster Vaccination

- A single booster dose of MENVEO may be administered to individuals aged 15 through 55 years who are at continued risk for meningococcal disease if at least 4 years have elapsed since a prior dose of a meningococcal (serogroups A, C, Y, W-135) conjugate vaccine. (2.4)

3 DOSAGE FORMS AND STRENGTHS

Solution for injection. A single dose is 0.5 mL. (3)

4 CONTRAINDICATIONS

Severe allergic reaction (e.g., anaphylaxis) to a previous dose of MENVEO, to any component of this vaccine, or to any other diphtheria toxoid-containing vaccine. (4)

5 WARNINGS AND PRECAUTIONS

- Syncope (fainting) has occurred in association with administration of MENVEO. Procedures should be in place to avoid injury from fainting. (5.2)
- Apnea following intramuscular vaccination has been observed in some infants born prematurely. A decision about when to administer MENVEO to an infant born prematurely should be based on consideration of the individual infant's medical status and the potential benefits and possible risks of vaccination. (5.5)

6 ADVERSE REACTIONS

- Common solicited adverse reactions (≥10%) among children initiating vaccination at 2 months of age and receiving the 4-dose series were tenderness (24% to 41%) and erythema at injection site (11% to 15%), irritability (42% to 57%), sleepiness (29% to 50%), persistent crying (21% to 41%), change in eating habits (17% to 23%), vomiting (5% to 11%), and diarrhea (8% to 16%). (6.1)
- Common solicited adverse reactions (≥10%) among children initiating vaccination at 7 months through 23 months of age and receiving the 2-dose series were tenderness (10% to 16%) and erythema at injection site (12% to 15%), irritability (27% to 40%), sleepiness (17% to 29%), persistent crying (12 to 21%), change in eating habits (12% to 20%), and diarrhea (10% to 16%). (6.1)
- Common solicited adverse reactions (≥10%) among children aged 2 through 10 years who received MENVEO were injection site pain (31%), erythema (23%), irritability (18%), induration (16%), sleepiness (14%), malaise (12%), and headache (11%). (6.1)
- Common solicited adverse reactions (≥10%) among adolescents and adults who received a single dose of MENVEO were pain at the injection site (41%), headache (30%), myalgia (18%), malaise (16%), and nausea (10%). Similar rates of solicited adverse reactions were observed following a single booster dose. (6.1)

To report SUSPECTED ADVERSE REACTIONS, contact GlaxoSmithKline at 1-888-825-5249 or VAERS at 1-800-822-7967 or www.vaers.hhs.gov.

FULL PRESCRIBING INFORMATION

1 INDICATIONS AND USAGE

MENVEO is a vaccine indicated for active immunization to prevent invasive meningococcal disease caused by Neisseria meningitidis serogroups A, C, Y, and W-135 in individuals 2 months through 55 years of age.

MENVEO does not prevent N. meningitidis serogroup B infections.

2 DOSAGE AND ADMINISTRATION

For intramuscular injection only.

2.1 MENVEO Presentations

MENVEO is supplied in two presentations, a two-vial presentation and a one-vial presentation.

Two-Vial Presentation

The two-vial presentation includes a vial with a gray cap containing the MenCYW-135 liquid conjugate component and a vial with an orange cap containing the MenA lyophilized conjugate component. The contents of the vials must be combined to form MENVEO prior to administration. This presentation is for use in individuals 2 months through 55 years of age.

One-Vial Presentation

The one-vial presentation contains MENVEO in a single vial with a pink cap and does not require reconstitution before use. This presentation is for use in individuals 10 through 55 years of age.

2.2 Preparation

Reconstitution Instructions for MENVEO Two-Vial Presentation

Use the MenCYW-135 liquid conjugate component (Vial 1, gray cap) to reconstitute the MenA lyophilized conjugate component (Vial 2, orange cap) to form MENVEO. Invert Vial 2 and shake well until the lyophilized conjugate component is dissolved. After reconstitution, withdraw 0.5 mL from the vial containing the reconstituted vaccine. See Figures 1 through 4.

Administer MENVEO immediately after reconstitution.

Figure 1. Cleanse both vial stoppers. Using a sterile needle and sterile graduated syringe, withdraw the entire contents of Vial 1 containing the MenCYW-135 liquid conjugate component while slightly tilting the vial.

Figure 2. Slowly transfer entire contents of the syringe into Vial 2 containing the MenA lyophilized conjugate component.

Figure 3. Invert the vial and shake well until lyophilized conjugate component is completely dissolved.

Figure 4. After reconstitution, withdraw 0.5 mL from the vial containing the reconstituted vaccine.

Instructions for MENVEO One-Vial Presentation

The MENVEO presentation that is supplied in a single vial with a pink cap does NOT require reconstitution. Withdraw 0.5 mL from the vial.

2.3 Administration

MENVEO is a clear, colorless solution, free from visible foreign particles. Parenteral drug products should be inspected visually for particulate matter and discoloration prior to administration, whenever solution and container permit. If any of these conditions exist, MENVEO should not be administered.

Administer a single 0.5-mL dose by intramuscular injection.

2.4 Dosing Schedule

The dosing schedule is as follows:

Primary Vaccination

Table 1. Dosing Schedule for MENVEO Primary Vaccination
MENVEO Two-Vial Presentation
Infants Aged 2 Months | 4-dose series at 2, 4, 6, and 12 months of age
Children Aged 7 through 23 Months | 2-dose series with the second dose administered in the second year of life and at least 3 months after the first dose
Children Aged 2 through 10 Years | A single dose; For children aged 2 through 5 years at continued high risk of meningococcal disease, a second dose may be administered 2 months after the first dose.
Adolescents and Adults Aged 11 through 55 Years | A single dose
MENVEO One-Vial Presentation
Adolescents and Adults Aged 10 through 55 Years | A single dose

Booster Vaccination

Adolescents and Adults Aged 15 through 55 Years: A single booster dose of MENVEO using either the two-vial presentation or the one-vial presentation may be administered to individuals who are at continued risk for meningococcal disease if at least 4 years have elapsed since a prior dose of a meningococcal (serogroups A, C, Y, W-135) conjugate vaccine.

3 DOSAGE FORMS AND STRENGTHS

MENVEO is a solution for intramuscular injection. A single dose is 0.5 mL.

4 CONTRAINDICATIONS

Do not administer MENVEO to individuals with a severe allergic reaction (e.g., anaphylaxis) to a previous dose of MENVEO, to any component of this vaccine, or to any other diphtheria toxoid-containing vaccine. [See Description (11).]

5 WARNINGS AND PRECAUTIONS

5.1 Management of Acute Allergic Reactions

Appropriate medical treatment must be available should an acute allergic reaction, including an anaphylactic reaction, occur following administration of MENVEO.

5.2 Syncope

Syncope (fainting) has occurred in association with administration of MENVEO. Procedures should be in place to avoid injury from fainting.

5.3 Altered Immunocompetence

Reduced Immune Response

Some individuals with altered immunocompetence, including some individuals receiving immunosuppressant therapy, may have reduced immune responses to MENVEO.

Complement Deficiency

Persons with certain complement deficiencies and persons receiving treatment that inhibits terminal complement activation (for example, eculizumab) are at increased risk for invasive disease caused by N. meningitidis, including invasive disease caused by serogroups A, C, Y, and W, even if they develop antibodies following vaccination with MENVEO. [See Clinical Pharmacology (12.1).]

5.4 Guillain-Barré Syndrome

Guillain-Barré syndrome (GBS) has been reported in temporal relationship following administration of another U.S.-licensed meningococcal quadrivalent polysaccharide conjugate vaccine. The decision by the healthcare professional to administer MENVEO to persons with a history of GBS should take into account the expected benefits and potential risks.

5.5 Apnea in Premature Infants

Apnea following intramuscular vaccination has been observed in some infants born prematurely. A decision about when to administer MENVEO to an infant born prematurely should be based on consideration of the individual infant's medical status and the potential benefits and possible risks of vaccination.

6 ADVERSE REACTIONS

6.1 Clinical Trials Experience

Because clinical trials are conducted under widely varying conditions, adverse reaction rates observed in clinical trials of a vaccine cannot be directly compared with rates in the clinical trials of another vaccine and may not reflect the rates observed in practice.

Overall, in clinical studies, 36,146 individuals 2 months through 55 years of age were administered at least one dose of MENVEO supplied in the two-vial presentation and 1,337 individuals 10 through 44 years of age were administered one dose of MENVEO supplied in the one-vial presentation. The safety data for the two-vial presentation are relevant to the safety of the one-vial presentation because each presentation contains the same meningococcal conjugated oligosaccharides. [See Description (11).]

Primary Vaccination Studies

Children Aged 2 through 23 Months: The safety of MENVEO in infants vaccinated at 2, 4, 6, and 12 months of age was evaluated in 3 randomized multicenter clinical studies (NCT00474526, NCT00806195, NCT01000311) conducted in the U.S., Australia, Canada, Taiwan, and several countries of Latin America in which 8,735 infants received at least 1 dose of MENVEO and routine infant vaccines (diphtheria toxoid; acellular pertussis; tetanus toxoid [DTaP]; inactivated polio types 1, 2, and 3 [IPV]; hepatitis B; Haemophilus influenzae type b (Hib) antigens; pentavalent rotavirus; and 7-valent pneumococcal conjugate [PCV7]). With Dose 4 of MENVEO, toddlers received concomitantly the following vaccines: 7-valent pneumococcal conjugate; measles, mumps, rubella, and varicella (MMRV); and inactivated hepatitis A. A total of 2,864 infants in these studies received the routine infant/toddler vaccines only. The infants who received MENVEO were Caucasian (33%), Hispanic (44%), African American (8%), Asian (8%), and other racial/ethnic groups (7%); 51% were male, with a mean age of 65.1 days (Standard Deviation [SD]: 7.5 days) at the time of first vaccination.

Safety data for administration of 2 doses of MENVEO in children aged 6 through 23 months are available from 3 randomized studies (NCT00474526, NCT00310856, NCT00626327) conducted in the U.S., Latin America, and Canada, of which one U.S. study specifically addressed the safety of MENVEO administered concomitantly with MMRV vaccine. The 1,985 older infants and toddlers who received 2 doses of MENVEO were Caucasian (49%), Hispanic (32%), African American (11%), and other racial/ethnic groups (8%), 51% male, with a mean age of 10.1 months (SD: 2.0 months).

Children Aged 2 through 10 Years: The safety of MENVEO in children aged 2 through 10 years was evaluated in 4 clinical trials (NCT00310817, NCT00262028, NCT00329849, NCT00616421) conducted in North America (66%), Latin America (28%), and Europe (6%) in which 3,181 subjects received MENVEO and 2,116 subjects received comparator vaccines (either Meningococcal Polysaccharide Vaccine, Groups A, C, Y, and W-135 Combined - MENOMUNE, Sanofi Pasteur [n = 861], or Meningococcal (Groups A, C, Y, and W-135) Polysaccharide Diphtheria Toxoid Conjugate Vaccine - MENACTRA, Sanofi Pasteur [n = 1,255]). The subjects aged 2 through 10 years who received MENVEO were Caucasian (69%), Hispanic (13%), African American (7%), and other racial/ethnic groups (6%), 51% male, with a mean age of 5.2 years. The safety of a second dose of MENVEO administered 2 months following a first dose was studied in 351 children aged 2 through 5 years.

Adolescents and Adults: The safety of MENVEO in individuals aged 11 through 55 years was evaluated in 5 randomized controlled clinical trials (NCT01018732, NCT00329901, NCT00450437, NCT00474487, NCT00518180) in which 6,185 participants received MENVEO alone (5,286 participants), MENVEO concomitant with other vaccine(s) (899 participants), or a U.S.-licensed comparator vaccine (1,966 participants). In the concomitant trials (NCT00329901, NCT00518180) MENVEO was given with vaccines containing: tetanus toxoid, diphtheria toxoid, and pertussis (Tdap), or Tdap with human papillomavirus (HPV). The comparator vaccine was either MENOMUNE (209 participants) or MENACTRA (1,757 participants). The trials were conducted in North America (46%), Latin America (41%), and Europe (13%). In 2 of the studies, subjects received concomitant vaccination with Tdap or with Tdap plus HPV. Overall, in these studies, subjects were Caucasian (50%), followed by Hispanic (40%), African American (7%), and other racial/ethnic groups (3%). Among recipients of MENVEO, 61%, 17%, and 22% were in the 11- through 18-year, 19- through 34-year, and 35- through 55-year age groups, respectively, with a mean age of 23.5 years (SD: 12.9 years). Among recipients of MENACTRA, 31%, 32%, and 37% were in the 11- through 18-year, 19- through 34-year, and 35- through 55-year age groups, respectively, with a mean age of 29.2 years (SD: 13.4 years). Among MENOMUNE recipients, 100% were in the 11- through 18-year age group, and the mean age was 14.2 years (SD: 1.8 years).

The safety of MENVEO one-vial presentation was evaluated in 2 randomized clinical trials (NCT03652610, NCT03433482). In these studies, 1,337 subjects aged 10 through 44 years were administered a single dose of MENVEO supplied in the one‑vial presentation and contributed to study analyses and 1,332 subjects 10 through 40 years of age were administered MENVEO supplied in the two-vial presentation. The studies were conducted in Australia, Belgium, Canada, Germany, and Italy (NCT03652610), and in Brazil, Estonia, Finland, France, Mexico, Russian Federation, South Africa, Spain, and Turkey (NCT03433482). Overall, in these studies, subjects were White (80.8%), followed by Hispanic or Latino ethnicity (12.8%), other racial groups (11.4%), African American (4.3%), Asian (3.0%), American Indian or Alaskan Native (0.3%), and Native Hawaiian or other Pacific Islander (0.1%). Overall, 25.6% of individuals were aged 10 through 17 years, and 74.4% were aged 18 through 44 years.

Booster Vaccination Study

In a multicenter, open-label trial (NCT02986854) conducted in the U.S., 601 subjects aged 15 to 51 years received a single booster dose of MENVEO 4 to 6 years after prior vaccination with MENVEO (n = 301; median age: 16 years) or MENACTRA (n = 300; median age: 16 years). Across booster groups of MENVEO, 81% of subjects were White and 50% were female.

In most trials, solicited local and systemic adverse reactions were monitored daily for 7 days following each (one or more) vaccination and recorded on a diary card. Participants were monitored for unsolicited adverse events which included adverse events requiring a physician visit or Emergency Department visit (i.e., medically-attended) or which led to a subject’s withdrawal from the study. Among children, adolescents, and adults aged 2 to 55 years, medically significant adverse events and serious adverse events (SAEs) were monitored for 6 months after vaccination. Across the studies of infants and toddlers aged 2 through 23 months, either all medically-attended or all medically-significant adverse events were collected in the period between the infant dose(s) and the toddler doses and during the 6-month period after the toddler dose.

Solicited Adverse Reactions in the Primary Vaccination Studies

The reported frequencies of solicited local and systemic adverse reactions from U.S. infants in the largest multinational safety study of MENVEO (NCT00806195) are presented in Table 2. Among the U.S. participants in the group receiving MENVEO with routine vaccines, 51% were female; 64% were Caucasian, 12% were African American, 15% were Hispanic, 2% were Asian, and 7% were of other racial/ethnic groups.

In infants initiating vaccination at 2 months of age and receiving the 4-dose series, common solicited adverse reactions (>10%) were tenderness (24% to 41%) and erythema at injection site (11% to 15%), irritability (42% to 57%), sleepiness (29% to 50%), persistent crying (21% to 41%), change in eating habits (17% to 23%), vomiting (5% to 11%), and diarrhea (8% to 16%). The rates of solicited adverse reactions reported for subjects aged 2 months and older receiving MENVEO with routine vaccines at 2, 4, 6, and 12 months of age were comparable to rates among subjects who only received routine vaccines.

Table 2. Rates of Solicited Adverse Reactions Reported in U.S. Infants, Aged 2 Months and Older, during the 7 Days following Each Vaccination of MENVEO Administered with Routine Infant/Toddler Vaccines, or Routine Infant/Toddler Vaccines Alone at 2, 4, 6, and 12 Months of Agea
Adverse Reactions | Dose 1 |  | Dose 2 |  | Dose 3 |  | Dose 4
Adverse Reactions | MENVEO with Routineb % | Routine Vaccinesb % | MENVEO with Routineb % | Routine Vaccinesb % | MENVEO with Routineb % | Routine Vaccinesb % | MENVEO with Routineb % | Routine Vaccinesb %
Local Adverse Reactionsc | n = 1,250-1,252 | n = 428 | n = 1,205-1,207 | n = 399 | n = 1,056-1,058 | n = 351-352 | n = 1,054-1,055 | n = 334-337
Tenderness, any | 41 | 45 | 31 | 36 | 24 | 32 | 29 | 39
Tenderness, severed | 3 | 5 | 2 | 2 | 1 | 3 | 1 | 1
Erythema, any | 11 | 14 | 12 | 21 | 14 | 23 | 15 | 25
Erythema,; >50 mm | <1 | <1 | 0 | 0 | 0 | 0 | 0 | 0
Induration, any | 8 | 16 | 9 | 17 | 8 | 19 | 8 | 21
Induration,; >50 mm | 0 | <1 | 0 | 0 | 0 | 0 | 0 | 0
Systemic Adverse Reactions | n = 1,246-1,251 | n = 427-428 | n = 1,119-1,202 | n = 396-398 | n = 1,050-1,057 | n = 349-350 | n = 1,054-1,056 | n = 333-337
Irritability, any | 57 | 59 | 48 | 46 | 42 | 38 | 43 | 42
Irritability, severee | 2 | 2 | 1 | 3 | 1 | 1 | 2 | 1
Sleepiness, any | 50 | 50 | 37 | 36 | 30 | 30 | 29 | 27
Sleepiness, severef | 2 | 1 | 1 | 1 | <1 | <1 | 1 | 0
Persistent crying, any | 41 | 38 | 28 | 24 | 22 | 17 | 21 | 18
Persistent crying,; ≥3 hours | 2 | 2 | 2 | 2 | 1 | 1 | 1 | 1
Change in eating habits, any | 23 | 24 | 18 | 17 | 17 | 13 | 19 | 16
Change in eating habits, severeg | 1 | 1 | 1 | 1 | 1 | <1 | 1 | 0
Vomiting, any | 11 | 9 | 7 | 6 | 6 | 4 | 5 | 4
Vomiting, severeh | <1 | 0 | <1 | 0 | <1 | 0 | <1 | 0
Diarrhea, any | 16 | 11 | 11 | 8 | 8 | 6 | 13 | 9
Diarrhea, severei | <1 | <1 | <1 | <1 | 1 | <1 | 1 | 1
Rashj | 3 | 3 | 3 | 4 | 3 | 3 | 4 | 3
Fever ≥38.0°Ck | 3 | 2 | 4 | 6 | 7 | 6 | 9 | 7
Fever 38.0-38.9°C | 3 | 2 | 4 | 5 | 7 | 6 | 6 | 5
Fever 39.0-39.9°C | 0 | 0 | 1 | 1 | <1 | 0 | 2 | 2
Fever ≥40.0°C | 0 | <1 | 0 | <1 | 0 | 0 | <1 | 0
NCT00806195.
n = Number of subjects who completed the diary card for a given symptom at the specified vaccination.
a As-Treated Safety Subpopulation = U.S. children who received at least 1 dose of study vaccine and whose diary cards were completed per protocol and returned to the site.
b Routine infant/toddler vaccines include DTaP-IPV-Hib and PCV7 at Doses 1, 2, 3, and PCV7, MMRV, and Hepatitis A vaccines at Dose 4. Hepatitis B (HBV) and rotavirus vaccines were allowed according to Advisory Committee on Immunization Practices (ACIP) recommendations.
c Local reactogenicity of MENVEO and PCV7 was assessed.
d Tenderness, severe = Cried when injected limb moved.
e Irritability, severe = Unable to console.
f Sleepiness, severe = Sleeps most of the time, hard to arouse.
g Change in eating habits, severe = Missed >2 feeds.
h Vomiting, severe = Little/no intake for more prolonged time.
i Diarrhea, severe = ≥6 liquid stools, no solid consistency.
j Rash was assessed only as present or not present, without a grading for severity.
k Axillary temperature.

The safety of a second dose of MENVEO administered at 12 months of age concomitantly with MMRV was investigated in a randomized, controlled, multicenter study (NCT00626327) conducted in the U.S. The rates of solicited adverse reactions reported were comparable between the concomitantly administered group (MENVEO with MMRV) and the group which received MMRV alone or MENVEO alone. The frequency and severity of solicited local and systemic reactions occurring within 7 days following vaccination at 12 months of age are shown in Table 3. In subjects who received both MENVEO and MMRV at 12 months of age local reactions at both injection sites were evaluated separately. Body temperature measurements were collected for 28 days following the 12-months-of-age visit, when MMRV was administered to the vaccinees. Common solicited adverse reactions (≥10%) among children initiating vaccination at 7 months through 23 months of age and receiving the 2-dose series were tenderness (10% to 16%) and erythema at injection site (12% to 15%), irritability (27% to 40%), sleepiness (17% to 29%), persistent crying (12% to 21%), change in eating habits (12% to 20%), and diarrhea (10% to 16%). An examination of the fever profile during this period showed that MENVEO administered with MMRV did not increase the frequency or intensity of fever above that observed for the MMRV-only group.

Table 3. Rates of Solicited Adverse Reactions Reported in U.S. Toddlers during the 7 Days following Vaccination with MENVEO Administered at 7-9 Months and 12 Months of Age, MENVEO Administered Alone at 7-9 Months and with MMRV at 12 Months of Age, and MMRV Administered Alone at 12 Months of Agea
Adverse Reactions | MENVEO |  | MENVEO + MMRV |  | MMRV
Adverse Reactions | MENVEO 7-9 Months % | MENVEO 12 Months % | MENVEO 7-9 Months % | MENVEO with MMRV 12 Months % | MMRV 12 Months %
Local Adverse Reactions– MENVEO | n = 460-462 | n = 381-384 | n = 430-434 | n = 386-387
Tenderness, any | 11 | 10 | 11 | 16 | N/A
Tenderness, severeb | <1 | <1 | <1 | 0 | N/A
Erythema, any | 15 | 13 | 13 | 12 | N/A
Erythema, >50 mm | <1 | <1 | 0 | 1 | N/A
Induration, any | 8 | 8 | 7 | 8 | N/A
Induration, >50 mm | <1 | <1 | 0 | 1 | N/A
Local Adverse Reactions– MMRV |  |  |  | n = 382-383 | n = 518-520
Tenderness, any | N/A | N/A | N/A | 16 | 19
Tenderness, severeb | N/A | N/A | N/A | 0 | <1
Erythema, any | N/A | N/A | N/A | 15 | 14
Erythema, >50 mm | N/A | N/A | N/A | 1 | <1
Induration, any | N/A | N/A | N/A | 13 | 8
Induration, >50 mm | N/A | N/A | N/A | <1 | 0
Systemic Adverse Reactions | n = 461-463 | n = 385-386 | n = 430-434 | n = 387-389 | n = 522-524
Irritability, any | 40 | 27 | 37 | 37 | 44
Irritability, severec | 2 | 2 | 2 | 1 | 3
Sleepiness, any | 26 | 17 | 29 | 26 | 32
Sleepiness, severed | 2 | 1 | 1 | 1 | 2
Persistent crying, any | 21 | 12 | 20 | 19 | 20
Persistent crying,; ≥3 hours | 2 | 1 | 1 | 1 | 2
Change in eating habits, any | 17 | 12 | 17 | 20 | 20
Change in eating habits, severee | <1 | 1 | 1 | 2 | 1
Vomiting, any | 9 | 6 | 9 | 6 | 6
Vomiting, severef | <1 | <1 | <1 | <1 | <1
Diarrhea, any | 16 | 10 | 15 | 15 | 20
Diarrhea, severeg | 2 | 1 | <1 | 1 | 2
Rashh | 3 | 5 | 6 | 6 | 8
Fever ≥38.0°Ci | 5 | 5 | 6 | 9 | 7
Fever 38.0-38.9°C | 3 | 3 | 5 | 7 | 7
Fever 39.0-39.9°C | 2 | 2 | 1 | 1 | 1
Fever ≥40.0°C | <1 | 1 | <1 | <1 | 0
NCT00626327.
MMRV = Measles, mumps, rubella, and varicella; n = Number of subjects who completed the diary card for a given symptom at the specified vaccination.
a As-Treated Safety Subpopulation = U.S. children who received at least 1 dose of study vaccine and whose diary cards were completed per protocol and returned to the site.
b Tenderness, severe = Cried when injected limb moved.
c Irritability, severe = Unable to console.
d Sleepiness, severe = Sleeps most of the time, hard to arouse.
e Change in eating habits, severe = Missed >2 feeds.
f Vomiting, severe = Little/no intake for more prolonged time.
g Diarrhea, severe = ≥6 liquid stools, no solid consistency.
h Rash was assessed only as present or not present, without a grading for severity.
i Axillary temperature.

In clinical trials of children aged 2 through 10 years (NCT00310817, NCT00262028, NCT00329849, NCT00616421), the most frequently occurring adverse reactions (>10%) among all subjects who received MENVEO were injection site pain (31%), erythema (23%), irritability (18%), induration (16%), sleepiness (14%), malaise (12%), and headache (11%). Among subjects aged 11 through 55 years, the most frequently occurring adverse reactions (>10%) among all subjects who received MENVEO were pain at the injection site (41%), headache (30%), myalgia (18%), malaise (16%), and nausea (10%).

The rates of solicited adverse reactions reported for subjects aged 2 through 5 years and 6 through 10 years who received a single dose of MENVEO or MENACTRA in a randomized, controlled, multicenter study (NCT00616421) conducted in the U.S. and Canada are shown in Table 4. Following a second dose of MENVEO administered to children aged 2 through 5 years, the most common solicited adverse reactions (≥10%) were pain at injection site (28%), erythema (22%), irritability (16%), induration (13%), and sleepiness (12%). The solicited adverse reactions from a separate randomized, controlled, multicenter study conducted in the U.S. in adolescents and adults (NCT00450437) are provided in Tables 5 and 6, respectively. In neither study were concomitant vaccines administered with the study vaccines.

Table 4. Rates of Solicited Adverse Reactions within 7 Days following a Single Vaccination in Children Aged 2 through 5 Years and 6 through 10 Years
Adverse Reactions | Participants Aged 2 through 5 Years
Adverse Reactions | MENVEO n = 693 % |  |  | MENACTRA n = 684 %
Adverse Reactions | Any | Moderate | Severe | Any | Moderate | Severe
Local Adverse Reactions
Injection site paina | 33 | 6 | 1 | 35 | 8 | 0.4
Erythemab | 27 | 5 | 1 | 25 | 3 | 0.3
Indurationb | 18 | 2 | 0.4 | 18 | 2 | 0.3
Systemic Adverse Reactionsc
Irritabilitya | 21 | 6 | 1 | 22 | 7 | 1
Sleepinessa | 16 | 3 | 1 | 18 | 5 | 1
Change in eatinga | 9 | 2 | 1 | 10 | 2 | 0.3
Diarrheaa | 7 | 1 | 0.1 | 8 | 1 | 0
Headachea | 5 | 1 | 0 | 6 | 1 | 0.3
Rashd | 4 | - | - | 5 | - | -
Arthralgiaa | 3 | 1 | 0.1 | 4 | 1 | 0
Vomitinga | 3 | 1 | 0.1 | 3 | 1 | 0
Fevere | 2 | 0.4 | 0 | 2 | 0.3 | 0
 | Participants Aged 6 through 10 Years
Adverse Reactions | MENVEO; n = 582; % |  |  | MENACTRA; n = 571; %
Adverse Reactions | Any | Moderate | Severe | Any | Moderate | Severe
Local Adverse Reactions
Injection site paina | 39 | 8 | 1 | 45 | 10 | 2
Erythemab | 28 | 5 | 1 | 22 | 2 | 0.2
Indurationb | 17 | 2 | 0.3 | 13 | 2 | 0
Systemic Adverse Reactionsc
Headachea | 18 | 3 | 1 | 13 | 2 | 1
Malaisea | 14 | 3 | 1 | 11 | 3 | 1
Myalgiaa | 10 | 2 | 1 | 10 | 2 | 1
Nauseaa | 8 | 2 | 1 | 6 | 2 | 0.4
Arthralgiaa | 6 | 1 | 0 | 4 | 1 | 0.4
Chillsa | 5 | 1 | 0 | 5 | 1 | 0.4
Rashd | 5 | - | - | 3 | - | -
Fevere | 2 | 1 | 0 | 2 | 0 | 0.4
NCT00616421.
a Moderate: Some limitation in normal daily activity, Severe: Unable to perform normal daily activity.
b Moderate: ≥50-100 mm, Severe: >100 mm.
c Different systemic reactions were solicited in different age groups.
d Rash was assessed only as present or not present, without a grading for severity.
e Fever grading: Any: ≥38°C, Moderate: 39-39.9°C, Severe: ≥40°C. Parents reported the use of antipyretic medication to treat or prevent symptoms in 11% and 13% of subjects aged 2 through 5 years, 9% and 10% of subjects aged 6 through 10 years for MENVEO and MENACTRA, respectively.

Table 5. Rates of Solicited Adverse Reactions within 7 Days following Vaccination in Individuals Aged 11 through 18 Years
Adverse Reactions | MENVEO n = 1,631 % |  |  | MENACTRA n = 539 %
Adverse Reactions | Any | Moderate | Severe | Any | Moderate | Severe
Local Adverse Reactions
Injection site paina | 44 | 9 | 1 | 53 | 11 | 1
Erythemab | 15 | 2 | 0.4 | 16 | 1 | 0
Indurationb | 12 | 2 | 0.2 | 11 | 1 | 0
Systemic Adverse Reactions
Headachea | 29 | 8 | 2 | 28 | 7 | 1
Myalgiaa | 19 | 4 | 1 | 18 | 5 | 0.4
Nauseaa | 12 | 3 | 1 | 9 | 2 | 1
Malaisea | 11 | 3 | 1 | 12 | 5 | 1
Chillsa | 8 | 2 | 1 | 7 | 1 | 0.2
Arthralgiaa | 8 | 2 | 0.4 | 6 | 1 | 0
Rashc | 3 | - | - | 3 | - | -
Feverd | 1 | 0.4 | 0 | 1 | 0 | 0
NCT00450437.
a Moderate: Some limitation in normal daily activity, Severe: Unable to perform normal daily activity.
b Moderate: ≥50-100 mm, Severe: >100 mm.
c Rash was assessed only as present or not present, without a grading for severity.
d Fever grading: Any: ≥38°C, Moderate: 39-39.9°C, Severe: ≥40°C.

Table 6. Rates of Solicited Adverse Reactions within 7 Days following Vaccination in Individuals Aged 19 through 55 Years
Adverse Reactions | MENVEO n = 1,018 % |  |  | MENACTRA n = 336 %
Adverse Reactions | Any | Moderate | Severe | Any | Moderate | Severe
Local Adverse Reactions
Injection site paina | 38 | 7 | 0.3 | 41 | 6 | 0
Erythemab | 16 | 2 | 1 | 12 | 1 | 0
Indurationb | 13 | 1 | 0.4 | 9 | 0.3 | 0
Systemic Adverse Reactions
Headachea | 25 | 7 | 2 | 25 | 7 | 1
Myalgiaa | 14 | 4 | 0.5 | 15 | 3 | 1
Malaisea | 10 | 3 | 1 | 10 | 2 | 1
Nauseaa | 7 | 2 | 0.4 | 5 | 1 | 0.3
Arthralgiaa | 6 | 2 | 0.4 | 6 | 1 | 1
Chillsa | 4 | 1 | 0.1 | 4 | 1 | 0
Rashc | 2 | - | - | 1 | - | -
Feverd | 1 | 0.3 | 0 | 1 | 0.3 | 0
NCT00450437.
a Moderate: Some limitation in normal daily activity, Severe: Unable to perform normal daily activity.
b Moderate: ≥50-100 mm, Severe: >100 mm.
c Rash was assessed only as present or not present, without a grading for severity.
d Fever grading: Any: ≥38°C, Moderate: 39-39.9°C, Severe: ≥40°C.

In studies NCT03652610 and NCT03433482, there were no notable differences in frequency and severity of solicited adverse reactions within 7 days following vaccination in individuals who received the one-vial presentation compared to individuals who received the two-vial presentation.

Solicited Adverse Reactions in the Booster Vaccination Study (Adolescents and Adults)

A multicenter, open-label clinical trial (NCT02986854) was conducted in the U.S. in subjects aged 15 through 55 years [see Clinical Studies (14.1)]. The methodology for evaluating solicited adverse reactions, unsolicited adverse events, and SAEs after a booster dose of MENVEO was similar to the primary vaccination studies. The most common solicited local and systemic adverse reactions within 7 days of vaccination were pain at injection site (36%) and fatigue (38%), respectively.

Solicited Adverse Reactions following Concomitant Vaccine Administration

The safety of 4-dose series of MENVEO administered concomitantly with U.S.-licensed routine infant and toddler vaccines was evaluated in one pivotal trial (NCT00806195). The safety of a 2-dose series of MENVEO initiated at 7-9 months of age, with the second dose administered concomitantly with U.S.-licensed MMRV vaccine at 12 months of age, was evaluated in one pivotal trial (NCT00626327). Rates of solicited adverse reactions which occurred 7 days following vaccination are shown in Tables 2 and 3, respectively. There was no significant increase in the rates of solicited systemic or local reactions observed in recipients of routine childhood vaccines when concomitantly vaccinated with MENVEO. [See Drug Interactions (7.1).]

The safety of MENVEO administered concomitantly with Tdap and HPV was evaluated in a single-center study (NCT00518180) conducted in Costa Rica. Solicited local and systemic adverse reactions were reported as noted above. In this study, subjects aged 11 through 18 years received MENVEO concomitantly with Tdap and HPV (n = 540), or MENVEO followed 1 month later by Tdap and then 1 month later by HPV (n = 541), or Tdap followed 1 month later by MENVEO and then 1 month later by HPV (n = 539). Some solicited systemic adverse reactions were more frequently reported in the group that received MENVEO, Tdap, and HPV concomitantly, (headache 40%, malaise 25%, myalgia 27%, and arthralgia 17%) compared with the group that first received MENVEO alone (headache 36%, malaise 20%, myalgia 19%, and arthralgia 11%). Among subjects administered MENVEO alone (1 month prior to Tdap), 36% reported headache, 20% malaise, and 16% myalgia. Among subjects administered MENVEO 1 month after Tdap, 27% reported headache, 18% malaise, and 16% myalgia.

Serious Adverse Events in All Safety Studies

SAEs in subjects receiving a 4-dose series of MENVEO at 2, 4, 6, and 12 months were evaluated in 3 randomized, multicenter clinical studies (NCT00474526, NCT00806195, NCT01000311). In the 2 controlled studies (NCT00806195, NCT01000311), the proportions of infants randomized to receive the 4-dose series of MENVEO concomitantly with routine vaccinations and infants who received routine vaccinations alone that reported SAEs during different study periods were, respectively: a) 2.7% and 2.2% during the infant series, b) 2.5% and 2.5% between the infant series and the toddler dose, c) 0.3% and 0.3% in the 1 month following the toddler dose, and d) 1.6% and 2.2% during the 6-month follow-up period after the last dose. In the third study (NCT00474526), which was controlled up to the toddler dose, the proportions of infants randomized to dosing regimens that included receiving 4 doses of MENVEO concomitantly with routine vaccinations at 2, 4, 6, and 12 months and infants who received routine vaccinations alone that reported SAEs during different study periods were, respectively: a) 3.5% and 3.6% during the infant series, and b) 2.8% and 3.3% between the infant series and the toddler dose, and c) 0.5% and 0.7% in the 1 month following the toddler dose. In the same study, 1.9% of infants randomized to receive the 4-dose series of MENVEO concomitantly with routine vaccinations reported SAEs during the 6-month follow-up period after the toddler dose. The most common SAEs reported in these 3 studies were wheezing, pneumonia, gastroenteritis, and convulsions, and most occurred at highest frequency after the infant series.

In a study of older infants (NCT00626327) randomized to receive the 2-dose series of MENVEO concomitantly with MMRV at 12 months of age, the rates of SAEs during the study, including the 6-month follow-up period after the last dose, were 3.6% and 3.8% for the groups receiving MENVEO with MMRV and MENVEO only, respectively. Infants receiving MMRV alone, who had a shorter period of study participation as they were enrolled at 12 months of age, had a lower rate of SAEs (1.5%). Among 1,597 study subjects included in the safety population, the most commonly reported SAEs in all study arms combined were dehydration (0.4%) and gastroenteritis (0.3%). Across the submitted studies of individuals aged 2 through 23 months within 28 days of vaccination, 2 deaths were reported in the groups receiving MENVEO (one case of sudden death and one case of sepsis), while no deaths were reported in the control group. None of the deaths was assessed as related to vaccination. Among subjects with symptom onset within 42 days of vaccination (Days 12, 25, 29), 3/12,049 (0.02%, 95% CI: [0.01%, 0.07%]) recipients of MENVEO and 0/2,877 (0%, 95% CI: [0%, 0.13%]) control recipients were diagnosed with Kawasaki Disease. One case of acute disseminated encephalomyelitis with symptom onset 29 days post Dose 4 was observed in a participant given MENVEO coadministered with routine U.S. childhood vaccines at 12 months of age (including measles, mumps, and rubella vaccine [MMR] and varicella vaccine).

The information regarding SAEs in subjects aged 2 through 10 years was derived from 3 randomized, controlled clinical trials (NCT00262028, NCT00329849, NCT00616421). Safety follow-up ranged from 6 through 12 months and included 2,883 subjects administered MENVEO. SAEs reported during the safety follow-up periods occurred in 21/2,883 (0.7%) subjects receiving MENVEO, in 7/1,255 (0.6%) MENACTRA subjects, and 2/861 (0.2%) MENOMUNE subjects. In the subjects receiving either 1 or 2 doses of MENVEO, there were 6 subjects with pneumonia, 3 subjects with appendicitis, and 2 subjects with dehydration; all other events were reported to occur in one subject. Among 1,255 subjects administered a single dose of MENACTRA and 861 subjects administered MENOMUNE, there were no events reported to occur in more than 1 subject. The SAEs occurring within the first 30 days after receipt of each vaccine were as follows: MENVEO (6/2,883 [0.2%]) — appendicitis, pneumonia, staphylococcal infection, dehydration, febrile convulsion, and tonic convulsion; MENACTRA (1/1255 [0.1%]) — inguinal hernia; MENOMUNE (2/861 [0.2%]) — abdominal pain, lobar pneumonia. In a supportive study (NCT00310817), 298 subjects received 1 or 2 doses of MENVEO and 22 (7%) had SAEs over a 13-month follow-up period including 13 subjects with varicella and 2 subjects with laryngitis. All other events were reported to occur in 1 subject. During the 30 days post vaccination in this study, 1 limb injury and 1 case of varicella were reported.

The information regarding SAEs in subjects aged 11 through 55 years was derived from 5 randomized, controlled clinical trials (NCT01018732, NCT00329901, NCT00450437, NCT00474487, NCT00518180). SAEs reported within 6 months of vaccination occurred in 40/6,185 (0.6%) subjects receiving MENVEO, 13/1,757 (0.7%) MENACTRA subjects, and 5/209 (2.4%) MENOMUNE subjects. During the 6 months following immunization, SAEs reported by more than 1 subject were as follows: MENVEO - appendicitis (3 subjects), road traffic accident (3 subjects), and suicide attempt (5 subjects); MENACTRA - intervertebral disc protrusion (2 subjects); MENOMUNE - none. SAEs that occurred within 30 days of vaccination were reported by 7 of 6,185 (0.1%) subjects in the group receiving MENVEO, 4 of 1,757 (0.2%) subjects in the MENACTRA group, and by none of 209 subjects in the MENOMUNE group. The events that occurred during the first 30 days post immunization with MENVEO were: vitello-intestinal duct remnant, Cushing’s syndrome, viral hepatitis, pelvic inflammatory disease, intentional multiple-drug overdose, simple partial seizure, and suicidal depression. The events that occurred during the first 30 days post immunization with MENACTRA were: herpes zoster, fall, intervertebral disc protrusion, and angioedema.

In the 2 clinical studies (NCT03652610, NCT03433482) which evaluated the safety of the one-vial presentation of MENVEO, SAEs were reported by 14 subjects (1.0%) who received the one-vial presentation of MENVEO and 14 subjects (1.1%) who received the two-vial presentation of MENVEO within the 6-month follow-up period after vaccination. No deaths were reported. None of the SAEs were related to the study vaccines.

6.2 Postmarketing Experience

In addition to reports in clinical trials, the following adverse reactions have been identified during postapproval use of MENVEO. Because these reactions are reported voluntarily from a population of uncertain size, it is not always possible to reliably estimate their frequency or establish a causal relationship to the vaccine.

Blood and Lymphatic System Disorders

Local lymphadenopathy.

Ear and Labyrinth Disorders

Hearing impaired, ear pain, vertigo, vestibular disorder.

Eye Disorders

Eyelid ptosis.

General Disorders and Administration Site Conditions

Injection site pruritus; pain; erythema; inflammation; and swelling, including extensive swelling of the vaccinated limb; fatigue; malaise; pyrexia.

Immune System Disorders

Hypersensitivity reactions, including anaphylaxis.

Infections and Infestations

Vaccination site cellulitis.

Injury, Poisoning, and Procedural Complications

Fall, head injury.

Investigation

Alanine aminotransferase increased, body temperature increased.

Musculoskeletal and Connective Tissue Disorders

Arthralgia, bone pain.

Nervous System Disorders

Dizziness, syncope, tonic convulsion, headache, facial paresis, balance disorder.

Respiratory, Thoracic, and Mediastinal Disorders

Oropharyngeal pain.

Skin and Subcutaneous Tissue Disorders

Skin exfoliation.

Postmarketing Observational Safety Study

In a postmarketing observational safety study conducted in a U.S. health maintenance organization, data from electronic health records of 48,899 persons aged 11 through 21 years were used to evaluate pre-specified events of interest following vaccination with MENVEO. Using a self-controlled case series method, Bell’s palsy showed a statistically significant increased risk in the period 1 to 84 days post vaccination compared with the control period, with an overall adjusted relative incidence of 2.9 (95% CI: 1.1-7.5). Among the 8 reported cases of Bell’s palsy, 6 cases occurred in persons who received MENVEO concomitantly with one or more of the following vaccines: Tdap, HPV, and Influenza vaccine. All reported Bell’s palsy cases resolved.

7 DRUG INTERACTIONS

7.1 Concomitant Administration with Other Vaccines

Do not mix MENVEO or any of its components with any other vaccine or diluent in the same syringe or vial.

In 2 clinical trials of infants initiating vaccination at 2 months of age (NCT00474526, NCT01000311), MENVEO was given concomitantly at 2, 4, and 6 months with routine infant vaccines: diphtheria toxoid; acellular pertussis; tetanus toxoid; inactivated polio types 1, 2, and 3; hepatitis B; Haemophilus influenzae type b antigens; pentavalent rotavirus; and 7-valent pneumococcal conjugate vaccine. For Dose 4 given at 12 months of age, MENVEO was given concomitantly with the following vaccines: 7-valent pneumococcal conjugate, MMRV, or measles, mumps, and rubella vaccine and varicella vaccine (MMR+V), and inactivated hepatitis A. In a clinical trial of older infants (aged 7 months and older) and toddlers (NCT00626327), MENVEO was administered concomitantly with MMRV or MMR+V vaccine(s) at 12 months of age. No immune interference was observed for the concomitantly administered vaccines, including most pneumococcal vaccine serotypes (post Dose 3); no immune interference was observed post Dose 4 for any pneumococcal vaccine serotypes (NCT00474526, NCT01000311). [See Clinical Studies (14.1).]

For children aged 2 through 10 years, no data are available to evaluate safety and immunogenicity of other childhood vaccines when administered concomitantly with MENVEO.

In a clinical trial in adolescents (NCT00518180), MENVEO was given concomitantly with the following: Tdap and HPV; no interference was observed in meningococcal immune responses when compared with MENVEO given alone. Lower geometric mean antibody concentrations (GMCs) for antibodies to the pertussis antigens filamentous hemagglutinin (FHA) and pertactin were observed when MENVEO was administered concomitantly with Tdap and HPV as compared with Tdap alone. [See Clinical Studies (14.1).]

7.2 Immunosuppressive Treatments

Immunosuppressive therapies, such as irradiation, antimetabolite medications, alkylating agents, cytotoxic drugs, and corticosteroids (when used in greater than physiologic doses) may reduce the immune response to MENVEO. [See Warnings and Precautions (5.3).] The immunogenicity of MENVEO has not been evaluated in persons receiving such therapies.

8 USE IN SPECIFIC POPULATIONS

8.1 Pregnancy

Risk Summary

All pregnancies have a risk of birth defect, loss, or other adverse outcomes. In the U.S. general population, the estimated background risk of major birth defects and miscarriage in clinically recognized pregnancies is 2% to 4% and 15% to 20%, respectively.

There are no adequate and well-controlled studies of MENVEO in pregnant women in the U.S. There was a pregnancy exposure registry conducted from 2014-2017 that included 82 subjects. Available data do not suggest an increased risk of major birth defects and miscarriage in women who received MENVEO within 28 days prior to conception or during pregnancy (see Data).

A developmental toxicity study was performed in female rabbits administered 0.5 mL (at each occasion) of MENVEO prior to mating and during gestation. A single human dose is 0.5 mL. This study revealed no adverse effects on fetal or pre-weaning development (see Data).

Data

Human Data: A pregnancy exposure registry (2014 to 2017) included 82 pregnancies with known outcomes with exposure within 28 days prior to conception or during pregnancy. Miscarriage was reported for 12.2% of pregnancies with exposure to MENVEO within 28 days prior to conception or during pregnancy (10/82). Major birth defects were reported for 3.6% of live born infants whose mothers were exposed within 28 days prior to conception or during pregnancy (2/55). The rates of miscarriage and major birth defects were consistent with estimated background rates.

Animal Data: In a developmental toxicity study, female rabbits were administered MENVEO by intramuscular injection on Days 29, 15, and 1 prior to mating and on Gestation Days 7 and 20. The total dose was 0.5 mL at each occasion (a single human dose is 0.5 mL). No adverse effects on pre-weaning development up to Postnatal Day 29 were observed. There were no vaccine-related fetal malformations or variations observed.

8.2 Lactation

Risk Summary

It is not known whether the vaccine components of MENVEO are excreted in human milk. Data are not available to assess the effects of MENVEO in the breastfed infant or on milk production/excretion.

The developmental and health benefits of breastfeeding should be considered along with the mother’s clinical need for MENVEO and any potential adverse effects on the breastfed child from MENVEO or from the underlying maternal condition. For preventive vaccines, the underlying maternal condition is susceptibility to disease prevented by the vaccine.

8.4 Pediatric Use

Safety and effectiveness of MENVEO in children aged younger than 2 months have not been established.

Safety and effectiveness of the one-vial presentation of MENVEO in children aged younger than 10 years have not been established. [See Dosage and Administration (2).]

For children 2 months through 9 years of age, only the two-vial presentation is approved for use. [See Dosage and Administration (2).]

8.5 Geriatric Use

Safety and effectiveness of MENVEO in adults aged 65 years and older have not been established.

11 DESCRIPTION

MENVEO [Meningococcal (Groups A, C, Y, and W-135) Oligosaccharide Diphtheria CRM197 Conjugate Vaccine] is a sterile liquid vaccine administered by intramuscular injection that contains N. meningitidis serogroup A, C, Y, and W-135 oligosaccharides conjugated individually to Corynebacterium diphtheriae CRM197 protein. The polysaccharides are produced by bacterial fermentation of N. meningitidis (serogroups A, C, Y, or W-135). N. meningitidis strains A, C, Y, and W-135 are each cultured and grown on Franz Complete medium and treated with formaldehyde. MenA, MenW-135, and MenY polysaccharides are purified by several extraction and precipitation steps. MenC polysaccharide is purified by a combination of chromatography and precipitation steps.

The protein carrier (CRM197) is produced by bacterial fermentation and is purified by a series of chromatography and ultrafiltration steps. C. diphtheriae is cultured and grown on CY medium containing yeast extracts and amino acids.

The oligosaccharides are prepared for conjugation from purified polysaccharides by hydrolysis, sizing, and reductive amination. After activation, each oligosaccharide is covalently linked to the CRM197 protein. The resulting glycoconjugates are purified to yield the 4 drug substances, which compose the final vaccine. The vaccine contains no preservative or adjuvant. Each dose of vaccine contains 10 mcg MenA oligosaccharide; 5 mcg of each of MenC, MenY, and MenW-135 oligosaccharides; and 25.9 to 64.1 mcg CRM197 protein. Residual formaldehyde per dose is estimated to be not more than 0.30 mcg.

The vials in which the vaccine components are contained are composed of Type I glass, USP.

The container closures (synthetic rubber stoppers) are not made with natural rubber latex.

12 CLINICAL PHARMACOLOGY

12.1 Mechanism of Action

Neisseria meningitidis is a gram-negative diplococcus that causes life-threatening invasive disease such as meningitis and sepsis. Globally, 5 serogroups, A, B, C, Y, and W-135 cause almost all invasive meningococcal infections. The presence of serum bactericidal antibodies protects against invasive meningococcal disease.^1 Vaccination with MENVEO leads to the production of bactericidal antibodies directed against the capsular polysaccharides of serogroups A, C, Y, and W-135.

13 NONCLINICAL TOXICOLOGY

13.1 Carcinogenesis, Mutagenesis, Impairment of Fertility

MENVEO has not been evaluated for carcinogenic or mutagenic potential, or for impairment of male fertility in animals. Vaccination of female rabbits with MENVEO had no effect on fertility. [See Use in Specific Populations (8.1).]

14 CLINICAL STUDIES

For all age groups, effectiveness has been inferred from the measurement of serogroup-specific anticapsular antibodies with bactericidal activity using pooled human serum that lacked bactericidal activity as the source of exogenous complement (hSBA).

14.1 Primary Vaccination Studies

In the absence of a licensed comparator vaccine for use in infants, the pre-specified endpoint for effectiveness of MENVEO in U.S. infants receiving a 4-dose series at 2, 4, 6, and 12 months of age was the proportion of subjects achieving an hSBA ≥1:8, with the lower limit of the 2-sided 95% CI for the point estimate being ≥80% of vaccinees for serogroup A, and ≥85% of vaccinees for serogroups C, W-135, and Y 1 month following the final dose.

The effectiveness of MENVEO in subjects aged 2 through 55 years was assessed by comparing the hSBA responses to immunization with MENVEO to those following immunization with the licensed meningococcal quadrivalent conjugate vaccine MENACTRA.

The primary effectiveness endpoint was hSBA seroresponse to each serogroup 28 days after vaccination. Seroresponse was defined as: a) post-vaccination hSBA ≥1:8 for subjects with a baseline hSBA <1:4; or, b) at least 4-fold higher than baseline titers for subjects with a pre-vaccination hSBA ≥1:4. Secondary endpoints included the proportion of subjects with post-vaccination hSBA ≥1:8 and the hSBA Geometric Mean Titer (GMT) for each serogroup. In a separate group of children aged 2 through 5 years randomized to receive 2 doses of MENVEO administered 2 months apart, seroresponse rate, proportion with post-vaccination hSBA ≥1:8, and GMT were determined for each serogroup.

Immunogenicity in Infants/Toddlers Aged 2 Months through 12 Months

The effectiveness of MENVEO in infants was assessed in a randomized, controlled, multicenter study (NCT01000311). Among the subjects receiving MENVEO who were included in the per-protocol analysis, the mean age at enrollment was 65 days, 51% were male, 67% were Caucasian, 6% were African American, 15% were Hispanic, 2% were Asian, and 9% were noted as other racial/ethnic groups. The pre-defined criteria for immunogenicity were met for all 4 serogroups A, C, W-135, and Y at 1 month following completion of a 4-dose series at 2, 4, 6, and 12 months of age (Table 7).

The percentage of subjects with hSBA ≥1:8 at 7 months was 94% to 98% for serogroups C, W-135, and Y and 76% for serogroup A.

Table 7. Bactericidal Antibody Responses following Administration of MENVEO with Routine Infant/Toddler Vaccines at 2, 4, 6, and 12 Months of Age
Serogroup |  | Post 3rd Dose | Post 4th Dose
A |  | n = 202 | n = 168
A | % ≥1:8; 95% CI | 76 (69, 81) | 89 (83a, 93)
A | GMT; 95% CI | 21; (17, 26) | 54; (44, 67)
C |  | n = 199 | n = 156
C | % ≥1:8; 95% CI | 94 (90, 97) | 95 (90a, 98)
C | GMT; 95% CI | 74; (62, 87) | 135; (107, 171)
W-135 |  | n = 194 | n = 153
W-135 | % ≥1:8; 95% CI | 98 (95, 99) | 97 (93a, 99)
W-135 | GMT; 95% CI | 79; (67, 92) | 215; (167, 227)
Y |  | n = 188 | n = 153
Y | % ≥1:8; 95% CI | 94 (89, 97) | 96 (92a, 99)
Y | GMT; 95% CI | 51; (43, 61) | 185; (148, 233)
NCT01000311.
% ≥1:8 = Proportions of subjects with hSBA ≥1:8 against a given serogroup; CI = Confidence interval; GMT = Geometric mean antibody titer; n = Number of infants eligible for inclusion in the Per-Protocol Immunogenicity population for whom serological results were available for the post-Dose 3 and post-Dose 4 evaluations.
Serum Bactericidal Assay with exogenous human complement source (hSBA).
a Pre-specified criteria for adequacy of immune response were met (lower limit of the 95% CI >80% for serogroup A and >85% for serogroups C, W, and Y).

The effectiveness of 2 doses of MENVEO given at 7-9 months and 12 months of age was assessed in a randomized, multicenter, controlled clinical trial (NCT00626327) conducted in the U.S. This study also investigated the concomitant administration of MENVEO and MMRV. The per-protocol population for assessing the response to 2 doses of MENVEO consisted of 386 subjects. Among subjects who completed the per-protocol analysis, their mean age at enrollment was 8.5 months (SD: 0.8 months), 50% were male; 61% were Caucasian, 15% were Hispanic, 10% were African American, 4% were Asian, and 10% were noted as other racial/ethnic groups.

Among the per-protocol population, after MENVEO administered at 7-9 and at 12 months, the proportions of subjects with hSBA ≥1:8 for serogroups A, C, W-135, and Y were respectively: 88% (84-91), 100% (98-100), 98% (96-100), 96% (93-99).

Immunogenicity in Children Aged 2 Years through 10 Years

Effectiveness in subjects aged 2 through 10 years was evaluated in a randomized, multicenter, active-controlled clinical study (NCT00616421) comparing hSBA responses following 1 dose of MENVEO or MENACTRA. The study was conducted in the U.S. and Canada and was stratified by age (2 through 5 years and 6 through 10 years). The per-protocol population evaluated after a single dose of vaccine consisted of 1,170 subjects who received MENVEO and 1,161 who received MENACTRA (Table 8) and included serological results for 89% to 95% of subjects, depending on serogroup and age group. Demographics for the 616 and 619 subjects aged 2 through 5 years for MENVEO and MENACTRA were as follows: mean age 3.6 years (SD: 1.1) vs. 3.6 years (SD: 1.1), 51% vs. 52% male, 62% vs. 62% Caucasian, 14% vs. 13% Hispanic, 12% vs. 13% African American, 6% vs. 4% Asian, and 7% vs. 8% other racial/ethnic groups, respectively. Demographics were for 554 and 542 per-protocol subjects aged 6 through 10 years for MENVEO and MENACTRA were as follows: mean age 7.9 years (SD: 1.4) vs. 8.1 years (SD: 1.4), 52% vs. 56% male, 66% vs. 66% Caucasian, 14% vs. 14% African American, 7% vs. 7% Hispanic, 5% vs. 6% Asian, and 8% vs. 8% other racial/ethnic groups, respectively. In a separate group of children aged 2 through 5 years randomized to receive 2 doses of MENVEO administered 2 months apart, the per-protocol population evaluated after 2 doses of MENVEO consisted of 297 subjects and included serologic results for 96% to 99% of subjects, depending on serogroup.

In study participants aged 2 through 5 years and 6 through 10 years, non-inferiority of MENVEO to MENACTRA for the proportion of subjects with a seroresponse was demonstrated for serogroups C, W-135, and Y, but not for serogroup A (Table 8).

Table 8. Comparison of Bactericidal Antibody Responsesa to MENVEO and MENACTRA 28 Days after Vaccination of Subjects Aged 2 through 5 Years and 6 through 10 Years
Endpoint by Serogroup | 2-5 Years |  |  | 6-10 Years
Endpoint by Serogroup | MENVEO (95% CI) | MENACTRA (95% CI) | Percent Difference (MENVEO – MENACTRA) or GMT Ratio (MENVEO/ MENACTRA) (95% CI) | MENVEO (95% CI) | MENACTRA (95% CI) | Percent Difference (MENVEO – MENACTRA) or GMT Ratio (MENVEO/ MENACTRA) (95% CI)
A | n = 606 | n = 611 |  | n = 551 | n = 541
% Seroresponseb | 72 (68, 75) | 77 (73, 80) | -5 (-10, -0)c | 77 (73, 80) | 83 (79, 86) | -6 (-11, -1)c
% ≥1:8 | 72 (68, 75) | 78 (74, 81) | -6 (-11, -1) | 77 (74, 81) | 83 (80, 86) | -6 (-11, -1)
GMT | 26 (22, 30) | 25 (21, 29) | 1.04 (0.86, 1.27) | 35 (29, 42) | 35 (29, 41) | 1.01 (0.83, 1.24)
C | n = 607 | n = 615 |  | n = 554 | n = 539
% Seroresponseb | 60 (56, 64) | 56 (52, 60) | 4 (-2, 9)d | 63 (59, 67) | 57 (53, 62) | 6 (0, 11)d
% ≥1:8 | 68 (64, 72) | 64 (60, 68) | 4 (-1, 10) | 77 (73, 80) | 74 (70, 77) | 3 (-2, 8)
GMT | 18 (15, 20) | 13 (11, 15) | 1.33 (1.11, 1.6) | 36 (29, 45) | 27 (21, 33) | 1.36 (1.06, 1.73)
W-135 | n = 594 | n = 605 |  | n = 542 | n = 533
% Seroresponseb | 72; (68, 75) | 58; (54, 62) | 14; (9, 19)d | 57 (53, 61) | 44 (40, 49) | 13 (7, 18)d
% ≥1:8 | 90; (87, 92) | 75; (71, 78) | 15; (11, 19) | 91; (88, 93) | 84; (81, 87) | 7; (3, 11)
GMT | 43; (38, 50) | 21; (19, 25) | 2.02; (1.71, 2.39) | 61; (52, 72) | 35; (30, 42) | 1.72; (1.44, 2.06)
Y | n = 593 | n = 600 |  | n = 545 | n = 539
% Seroresponseb | 66 (62, 70) | 45 (41, 49) | 21 (16, 27)d | 58 (54, 62) | 39 (35, 44) | 19 (13, 24)d
% ≥1:8 | 76 (72, 79) | 57 (53, 61) | 19 (14, 24) | 79 (76, 83) | 63 (59, 67) | 16 (11, 21)
GMT | 24 (20, 28) | 10 (8.68, 12) | 2.36 (1.95, 2.85) | 34 (28, 41) | 14 (12, 17) | 2.41 (1.95, 2.97)
NCT00616421.
a Serum Bactericidal Assay with exogenous human complement source (hSBA).
CI = Confidence interval; GMT = Geometric mean antibody titer.
b Seroresponse was defined as: Subjects with a pre-vaccination hSBA <1:4, a post-vaccination titer of >1:8 and among subjects with a pre-vaccination hSBA ≥1:4, a post-vaccination titer at least 4-fold higher than baseline.
c Non-inferiority criterion not met (the lower limit of the 2-sided 95% CI ≤-10% for vaccine group differences).
d Non-inferiority criterion met (the lower limit of the 2-sided 95% CI >-10% for vaccine group differences [MENVEO minus MENACTRA]).

In the 297 per-protocol subjects aged 2 through 5 years observed at 1 month after the second dose of MENVEO, the proportions of subjects with seroresponse (95% CI) were: 91% (87-94), 98% (95-99), 89% (85-92), and 95% (91-97) for serogroups A, C, W-135, and Y, respectively. The proportion of subjects with hSBA ≥1:8 (95% CI) were 91% (88-94), 99% (97-100), 99% (98-100), and 98% (95-99) for serogroups A, C, W-135, and Y, respectively. The hSBA GMTs (95% CI) for this group were 64 (51-81), 144 (118-177), 132 (111-157), and 102 (82-126) for serogroups A, C, W-135, and Y, respectively.

Immunogenicity in Adolescents Aged 11 Years through 18 Years

Effectiveness in subjects aged 11 through 55 years was evaluated in a randomized, multicenter, active-controlled clinical study (NCT00450437) comparing the hSBA responses following 1 dose of MENVEO or MENACTRA. The study was conducted in the U.S. and stratified by age (11 through 18 years and 19 through 55 years). This study enrolled 3,539 participants, who were randomized to receive a dose of MENVEO (n = 2,663) or MENACTRA (n = 876). Among subjects who completed the per-protocol evaluation for immunogenicity (n = 3,393, MENVEO = 2,549, MENACTRA = 844), demographics for subjects receiving MENVEO and MENACTRA, respectively, were as follows: mean age 23.9 (SD: 13.6) vs. 23.7 (SD: 13.7), 42% vs. 42% male, 79% vs. 78% Caucasian, 8% vs. 9% African American, 7% vs. 7% Hispanic, 3% vs. 3% Asian, 2% vs. 3% other racial/ethnic groups. Immunogenicity for each serogroup was assessed in a subset of study participants (Tables 9 and 10).

In study participants aged 11 through 18 years, non-inferiority of MENVEO to MENACTRA was demonstrated for all 4 serogroups for the proportion of subjects with a seroresponse (Table 9).

Table 9. Comparison of Bactericidal Antibody Responsesa to MENVEO and MENACTRA 28 Days after Vaccination of Subjects Aged 11 through 18 Years
Endpoint by Serogroup | Bactericidal Antibody Responsea |  | Comparison of MENVEO and MENACTRA
Endpoint by Serogroup | MENVEO (95% CI) | MENACTRA (95% CI) | MENVEO/ MENACTRA (95% CI) | MENVEO minus MENACTRA (95% CI)
A | n = 1,075 | n = 359
% Seroresponseb | 75; (72, 77) | 66; (61, 71) |  | 8; (3, 14)c
% >1:8 | 75 (73, 78) | 67 (62, 72) | - | 8; (3, 14)
GMT | 29; (24, 35) | 18; (14, 23) | 1.63; (1.31, 2.02) | -
C | n = 1,396 | n = 460
% Seroresponseb | 76; (73, 78) | 73; (69, 77) |  | 2; (-2, 7)c
% >1:8 | 85 (83, 87) | 85 (81, 88) | - | 0; (-4, 4)
GMT | 50 (39, 65) | 41 (30, 55) | 1.22; (0.97, 1.55) | -
W-135 | n = 1,024 | n = 288
% Seroresponseb | 75; (72, 77) | 63; (57, 68) |  | 12; (6, 18)c
% >1:8 | 96 (95, 97) | 88 (84, 92) | - | 8; (4, 12)
GMT | 87 (74, 102) | 44 (35, 54) | 2.00; (1.66, 2.42) | -
Y | n = 1,036 | n = 294
% Seroresponseb | 68; (65, 71) | 41; (35, 47) |  | 27; (20, 33)c
% >1:8 | 88 (85, 90) | 69 (63, 74) | - | 19; (14, 25)
GMT | 51 (42, 61) | 18 (14, 23) | 2.82; (2.26, 3.52) | -
NCT00450437.
CI = Confidence interval; GMT = Geometric mean antibody titer.
a Serum Bactericidal Assay with exogenous human complement source (hSBA).
b Seroresponse was defined as: a) post-vaccination hSBA ≥1:8 for subjects with a pre-vaccination hSBA <1:4; or, b) at least 4-fold higher than baseline titers for subjects with a pre-vaccination hSBA ≥1:4.
c Non-inferiority criterion for the primary endpoint met (the lower limit of the 2-sided 95% CI >-10% for vaccine group differences [MENVEO minus MENACTRA]).

Immunogenicity in Adults Aged 19 Years through 55 Years

The study in subjects aged 11 through 55 years was a randomized, multicenter, active-controlled clinical trial (NCT00450437) conducted in the U.S. and stratified by age (11 through 18 years and 19 through 55 years) as described above.

In study participants aged 19 through 55 years, non-inferiority of MENVEO to MENACTRA was demonstrated for all 4 serogroups for the proportion of subjects with a seroresponse (Table 10).

Table 10. Comparison of Bactericidal Antibody Responses to MENVEO and MENACTRA 28 Days after Vaccination of Subjects Aged 19 through 55 Years
Endpoint by Serogroup | Bactericidal Antibody Responsea |  | Comparison of MENVEO and MENACTRA
Endpoint by Serogroup | MENVEO (95% CI) | MENACTRA (95% CI) | MENVEO/ MENACTRA (95% CI) | MENVEO minus MENACTRA (95% CI)
A | n = 963 | n = 321
% Seroresponseb | 67; (64, 70) | 68; (63, 73) |  | -1; (-7, 5)c
% >1:8 | 69 (66, 72) | 71 (65, 76) | - | -2; (-7, 4)
GMT | 31 (27, 36) | 30 (24, 37) | 1.06; (0.82, 1.37) | -
C | n = 902 | n = 300
% Seroresponseb | 68; (64, 71) | 60; (54, 65) |  | 8; (2, 14)c
% >1:8 | 80 (77, 83) | 74 (69, 79) | - | 6; (1, 12)
GMT | 50 (43, 59) | 34 (26, 43) | 1.50; (1.14, 1.97) | -
W-135 | n = 484 | n = 292
% Seroresponseb | 50; (46, 55) | 41; (35, 47) |  | 9; (2, 17)c
% >1:8 | 94 (91, 96) | 90 (86, 93) | - | 4; (0, 9)
GMT | 111 (93, 132) | 69 (55, 85) | 1.61; (1.24, 2.1) | -
Y | n = 503 | n = 306
% Seroresponseb | 56; (51, 60) | 40; (34, 46) |  | 16; (9, 23)c
% >1:8 | 79 (76, 83) | 70 (65, 75) | - | 9; (3, 15)
GMT | 44 (37, 52) | 21 (17, 26) | 2.10; (1.60, 2.75) | -
NCT00450437.
CI = Confidence interval; GMT = Geometric mean antibody titer.
a Serum Bactericidal Assay with exogenous human complement source (hSBA).
b Seroresponse was defined as: a) post-vaccination hSBA >1:8 for subjects with a pre-vaccination hSBA <1:4; or, b) at least 4-fold higher than baseline titers for subjects with a pre-vaccination hSBA ≥1:4.
c Non-inferiority criterion for the primary endpoint met (the lower limit of the 2-sided 95% CI >-10% for vaccine group differences [MENVEO minus MENACTRA]).

Immunogenicity of MENVEO One-Vial Presentation in Individuals Aged 10 Years through 40 Years

Immunogenicity of MENVEO one-vial presentation was evaluated in an observer-blind randomized, multicenter, controlled clinical trial in individuals aged 10 to 40 years (NCT03433482). The study compared the immune response of the MENVEO one-vial presentation to the MENVEO two-vial presentation.

The primary analysis demonstrated non-inferiority of MenA serogroup hSBA GMTs at 28 days post-vaccination for the MENVEO one-vial presentation group compared to the MENVEO two-vial presentation group (lower limit of the two-sided 95% CI for the ratio of hSBA GMTs against serogroup A between the MENVEO one-vial presentation group and the MENVEO two-vial presentation group was greater than 0.5). Secondary analyses showed comparable immune responses against N. meningitidis serogroups C, W-135 and Y as measured by hSBA GMTs. Additional secondary analyses demonstrated comparable percentages of subjects with hSBA titers ≥8, and percentages of subjects with a ≥4-fold rise in titers compared to baseline for serogroups A, C, W-135 and Y.

14.2 Booster Vaccination Study

Immunogenicity in Adolescents and Adults Aged 15 Years through 55 Years

For a description of study design and number of participants, see section 6.1 Booster Vaccination Study. The co-primary immunogenicity endpoints were hSBA seroresponse to each serogroup 29 days a) following a booster vaccination with MENVEO given to subjects who received a prior dose of MENVEO, and b) following a booster vaccination with MENVEO given to subjects who received a prior dose of MENACTRA. Seroresponse was defined as: a) post-vaccination hSBA ≥1:16 for subjects with a baseline hSBA <1:4 or b) at least 4-fold higher than baseline titers for subjects with a pre-vaccination hSBA ≥1:4. Secondary endpoints included the proportions of subjects with post-vaccination hSBA ≥1:8, the hSBA GMTs for each serogroup, and antibody titers against each serogroup 4 to 6 years after a prior dose (as measured by percentages of subjects with hSBA titers ≥1:8 and hSBA GMTs prior to booster vaccination).

Seroresponse rates at Day 29 following a booster vaccination with MENVEO were 97% for serogroup A, 95% for serogroup C, 96% for serogroup W-135, and 97% for serogroup Y, in subjects who had received a prior dose of MENVEO (n = 290). At Day 6, following a booster vaccination, seroresponse rates were 39%, 51%, 50%, and 49% for serogroups A, C, W-135, and Y, respectively, in subjects who had received a prior dose of MENVEO.

The hSBA GMTs were 13, 92, 112, and 63 for serogroups A, C, W-135, and Y at Day 6, and 210, 1160, 1395, and 1067, respectively, for the 4 serogroups at Day 29 following a booster dose of MENVEO.

Overall, similar seroresponse rates and GMTs were observed for those subjects who received a booster vaccination with MENVEO following a prior dose of MENACTRA (n = 282).

Prior to booster vaccination, the percentage of subjects with hSBA titers >1:8 for serogroups A, C, W-135, and Y were 12%, 62%, 76%, and 54% for those who received a prior dose of MENVEO 4 to 6 years earlier, and 15%, 54%, 77%, and 47% for those who received a prior dose of MENACTRA 4 to 6 years earlier. The hSBA GMTs for serogroups A, C, W-135, and Y prior to booster vaccination were 3, 16, 23, and 9 following a prior vaccination with MENVEO and 3, 11, 23, and 8 following a prior vaccination with MENACTRA.

14.3 Immunogenicity of Concomitantly Administered Vaccines

In U.S. infants (NCT00474526, NCT01000311) who received MENVEO concomitantly with DTaP-IPV-Hib and PCV7 at 2, 4, and 6 months of age and hepatitis B vaccine (HBV) administered according to ACIP recommendations, there was no evidence for reduced antibody response to pertussis antigens (GMC to pertussis toxin, filamentous hemagglutinin, fimbriae, and pertactin), diphtheria toxoid (antibody levels ≥0.1 IU/mL), tetanus toxoid (antibody levels ≥0.1 IU/mL), poliovirus types 1, 2, and 3 (neutralizing antibody levels ≥1:8 to each virus), Haemophilus influenzae type b (anti-PRP antibody ≥0.15 mcg/mL), hepatitis B (anti-hepatitis B surface antigen ≥10 mIU/mL), or most serotypes of PCV7 (antibody levels ≥0.35 mcg/mL) relative to the response in infants administered DTaP-IPV-Hib, PCV7, and HBV. The immune responses to DTaP-IPV-Hib, PCV7, and HBV were evaluated 1 month following Dose 3. No interference was observed for pertussis based on GMC ratios, or for the other concomitantly administered vaccines, with the exception of pneumococcal serotype 6B and 23F, for which interference was suggested post Dose 3. No interference was observed post Dose 4 for these serotypes.

There was no evidence for interference in the immune response to MMR and varicella vaccines (among initially seronegative children) in terms of percentages of children with anti-measles antibodies ≥255 mIU/mL, anti-mumps ≥10 ELISA antibody units, anti-rubella ≥10 IU/mL, and anti-varicella ≥5 gp ELISA units/mL, administered at 12 months of age (NCT00626327) concomitantly with MENVEO relative to these vaccines administered alone. The immune responses to MMR and varicella vaccines were evaluated 6 weeks post vaccination.

For children aged 2 through 10 years, no data are available for evaluating safety and immunogenicity of other childhood vaccines when administered concomitantly with MENVEO.

For individuals aged 11 through 18 years, the effect of concomitant administration of MENVEO with Tdap and HPV was evaluated in a study (NCT00518180) conducted in Costa Rica (see also section 6.1 for the safety results from this trial). Subjects were randomized to receive one of the following regimens at the start of the trial: MENVEO plus Tdap plus HPV (n = 540); MENVEO alone (n = 541); Tdap alone (n = 539). Subjects were healthy adolescents aged 11 through 18 years (mean age between groups was 13.8 to 13.9 years). For antigens of MENVEO, the proportion (95% CI) of subjects achieving an hSBA seroresponse among those who received MENVEO plus Tdap plus HPV vs. MENVEO alone, respectively, were: serogroup A 80% (76, 84) vs. 82% (78, 85); serogroup C 83% (80, 87) vs. 84% (80, 87); serogroup W-135 77% (73, 80) vs. 81% (77, 84); serogroup Y 83% (79, 86) vs. 82% (79, 86). Among subjects who received Tdap plus MENVEO plus HPV, compared with Tdap alone, the proportions (95% CI) of subjects who achieved an anti-tetanus or anti-diphtheria toxoids levels ≥1.0 IU/mL in the 2 groups, respectively, were 100% (99, 100) vs. 98% (96, 99) and 100% (99, 100) vs. 100% (99, 100). For pertussis antigens, among subjects who received Tdap plus MENVEO plus HPV, compared with Tdap alone, the responses respectively for anti-pertussis toxin GMCs (95% CI) were 51 (47, 55) vs. 63 (58, 69) ELISA Units (EU)/mL, for anti-filamentous hemagglutinin were 342 (310, 376) vs. 511 (464, 563) EU/mL, and for anti-pertactin were 819 (727, 923) vs. 1,197 (1,061, 1,350) EU/mL. Because there are no established serological correlates of protection for pertussis, the clinical implications of the lower pertussis antigen responses are unknown.

15 REFERENCES

1. Goldschneider I, Gotschlich EC, Artenstein MS. Human immunity to the meningococcus. I. The role of humoral antibodies. J Exp Med. (1969);129:1307-1326.

16 HOW SUPPLIED/STORAGE AND HANDLING

16.1 MENVEO Two-Vial Presentation

MENVEO two-vial presentation is supplied in cartons containing:

- 5 Vials containing MenCYW-135 Liquid Conjugate Component (Vial 1; gray cap)
- 5 Vials containing MenA Lyophilized Conjugate Component (Vial 2; orange cap)

One vial of MenCYW-135 liquid conjugate component (Vial 1) and one vial of MenA lyophilized conjugate component (Vial 2) must be combined before use to form a single dose (0.5 mL) of MENVEO (packaged without syringes or needles). Each carton contains 5 doses of MENVEO.

The container closures (synthetic rubber stoppers) are not made with natural rubber latex.

Table 11. MENVEO: Two-Vial Presentation
Presentation | Carton NDC Number | MenCYW-135 Liquid Conjugate Component (Vial 1; gray cap) NDC Number | MenA Lyophilized Conjugate Component (Vial 2; orange cap) NDC Number
Carton of 10 vials (5 doses) | NDC 58160-955-09 | 5 Vials; NDC 58160-959-01 | 5 Vials; NDC 58160-958-01

Storage before Reconstitution

Do not freeze. Frozen/previously frozen product should be discarded.

Store refrigerated, away from the freezer compartment, at 36°F to 46°F (2°C to 8°C).

Protect from light. Vaccine must be maintained at 36°F to 46°F (2°C to 8°C) during transport.

Do not use after the expiration date.

16.2 MENVEO One-Vial Presentation

MENVEO one-vial presentation is supplied in cartons containing:

- 10 Vials containing MENVEO (pink cap)

Each carton contains 10 single dose vials of MENVEO. Each dose is 0.5 mL.

The container closures (synthetic rubber stoppers) are not made with natural rubber latex.

Table 12. MENVEO: One-Vial Presentation

Presentation | Carton NDC Number | MENVEO (pink cap) NDC Number
Carton of 10 vials; (10 doses) | NDC 58160-827-30 | 10 Vials; NDC 58160-827-03

Do not freeze. Frozen/previously frozen product should be discarded.

Store refrigerated, away from the freezer compartment, at 36°F to 46°F (2°C to 8°C).

Protect from light. Vaccine must be maintained at 36°F to 46°F (2°C to 8°C) during transport.

Do not use after the expiration date.

17 PATIENT COUNSELING INFORMATION

Give the recipient, parent, or guardian the Vaccine Information Statements, which are required by the National Childhood Vaccine Injury Act of 1986 to be given prior to immunization. These materials are available free of charge at the Centers for Disease Control and Prevention (CDC) website (www.cdc.gov/vaccines).

Provide the following information to the vaccine recipient, parent, or guardian:

- Potential benefits and risks of immunization with MENVEO.
- The importance of completing the immunization series.
- Potential for adverse reactions that have been temporally associated with administration of MENVEO or other vaccines containing similar components.
- Reporting any adverse reactions to their healthcare provider.

MENVEO is a trademark owned by or licensed to the GSK group of companies.

The other brands listed are trademarks owned by or licensed to their respective owners and are not owned by or licensed to the GSK group of companies. The makers of these brands are not affiliated with and do not endorse the GSK group of companies or its products.

Manufactured by:
GSK Vaccines, Srl
Bellaria-Rosia 53018, Sovicille (SI), Italy
US License No. 1617
Distributed by:
GlaxoSmithKline
Durham, NC 27701
©2025 GSK group of companies or its licensor.
MNV:10PI

PACKAGE LABEL

PRINCIPAL DISPLAY PANEL

NDC 58160-955-09

MENVEO

MENINGOCOCCAL (GROUPS A, C, Y and W-135)

Oligosaccharide Diphtheria CRM197 Conjugate Vaccine

Men-ACYW

Rx Only

2-vial Presentation: A vial containing the MenCYW-135 liquid conjugate component and a vial containing the MenA lyophilized conjugate component. The contents of the vials must be combined to form MENVEO prior to administration.

2 Months through 55 Years of Age

2-Vial Presentation

Contents (5 doses of MENVEO):

5 Vials containing MenCYW-135 Liquid Conjugate Component (Vial 1)

5 Vials containing MenA Lyophilized Conjugate Component (Vial 2)

After reconstitution, a single dose of MENVEO is 0.5 mL

MENVEO

MenA Lyophilized Conjugate Component Made in Germany

MenCYW-135 Liquid Conjugate Component Made in Italy

©2025 GSK group of companies or its licensor.

Rev. 12/25

526471

PRINCIPAL DISPLAY PANEL - Vial Label

NDC 58160-958-01

MenA Lyophilized Conjugate Component

515154

PRINCIPAL DISPLAY PANEL - Vial Label

NDC 58160-959-01

MenCYW-135 Liquid Conjugate Component

515155

PACKAGE LABEL

PRINCIPAL DISPLAY PANEL

NDC 58160-827-30

MENVEO

Meningococcal (Groups A, C, Y and W-135)

Oligosaccharide Diphtheria CRM197 Conjugate Vaccine

Men-ACYW

Rx Only

1-Vial Presentation

DO NOT RECONSTITUE.

10 Years through 55 Years of Age

1-Vial Presentation

1Dose

Contents (10 doses of MENVEO):

10 Vials containing MenACYW-135 Liquid Vaccine

A single dose of MENVEO is 0.5 mL

GSK

MENVEO

Made in Italy

©2024 GSK group of companies or its licensor.

Rev. 08/24

520906

PACKAGE LABEL

PRINCIPAL DISPLAY PANEL

NDC 58160-827-03

MENVEO

Meningococcal (Groups A, C, Y AND W-135)

Oligosaccharide Diphtheria CRM197 Conjugate Vaccine

DO NOT RECONSTITUTE

10 Years through 55 Years of Age

0.5-mL Single Dose

Mfd. By GSK Vaccines, Srl

Vial 1 of 1

Rx Only

Rev. 10/22

511891